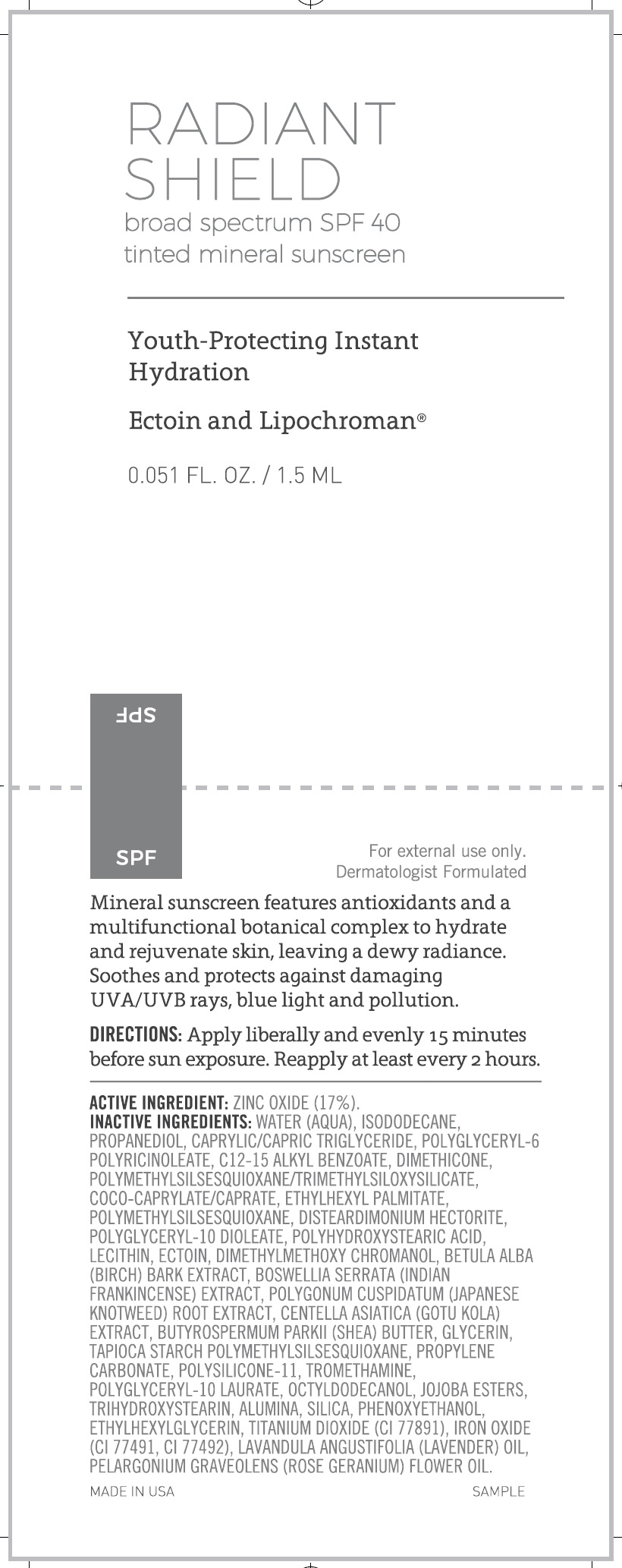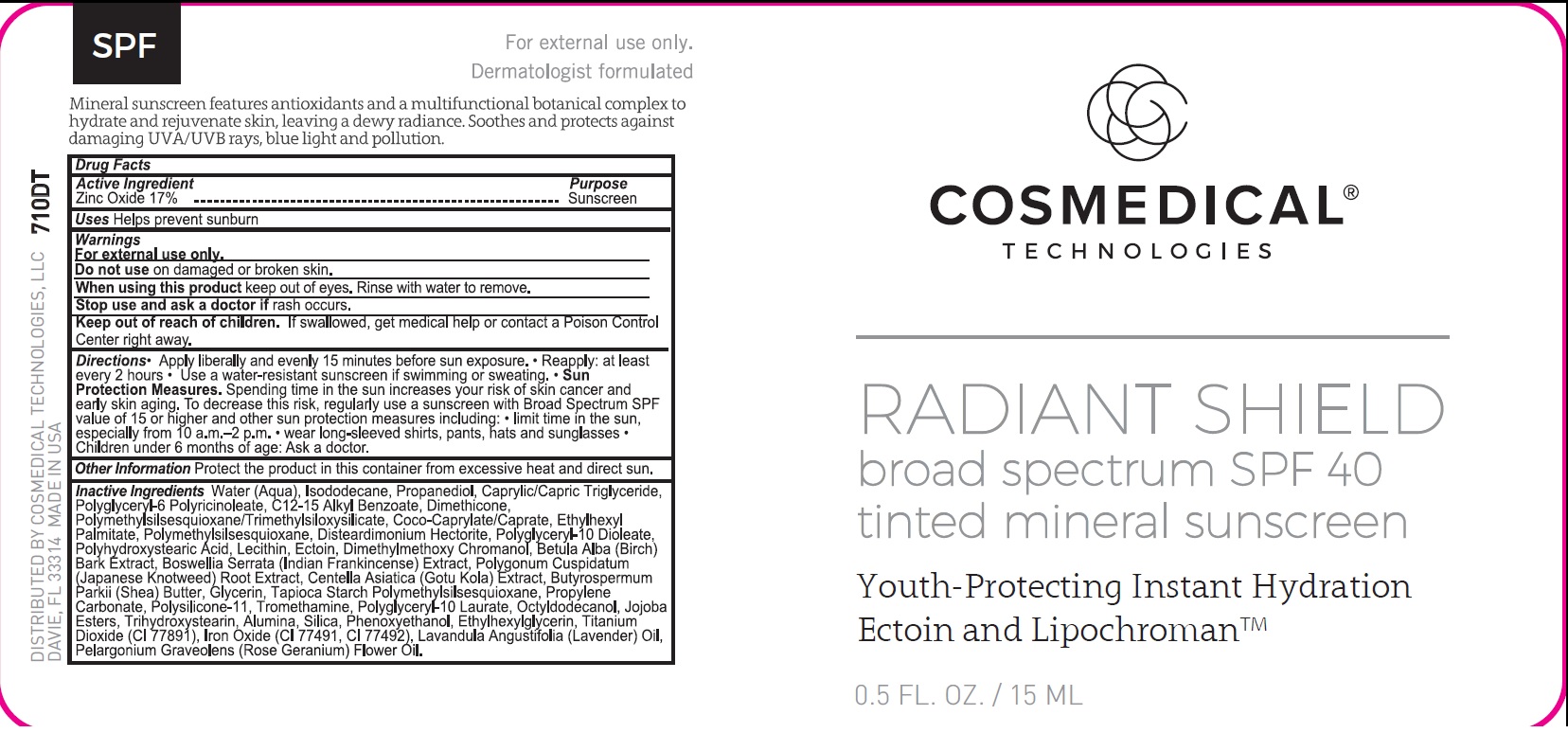 DRUG LABEL: Radiant Shield Tinted Mineral Sunscreen SPF 40
NDC: 70060-1510 | Form: CREAM
Manufacturer: CosMedical Technologies, LLC
Category: otc | Type: HUMAN OTC DRUG LABEL
Date: 20250919

ACTIVE INGREDIENTS: ZINC OXIDE 170 mg/1 mL
INACTIVE INGREDIENTS: WATER; ISODODECANE; PROPANEDIOL; MEDIUM-CHAIN TRIGLYCERIDES; POLYGLYCERYL-6 POLYRICINOLEATE; ALKYL (C12-15) BENZOATE; DIMETHICONE; POLYMETHYLSILSESQUIOXANE (4.5 MICRONS); COCOYL CAPRYLOCAPRATE; ETHYLHEXYL PALMITATE; DISTEARDIMONIUM HECTORITE; POLYGLYCERYL-10 DIOLEATE; ECTOINE; DIMETHYLMETHOXY CHROMANOL; BETULA PUBESCENS BARK; INDIAN FRANKINCENSE; REYNOUTRIA JAPONICA ROOT; CENTELLA ASIATICA TRITERPENOIDS; SHEA BUTTER; GLYCERIN; PROPYLENE CARBONATE; DIMETHICONE/VINYL DIMETHICONE CROSSPOLYMER (SOFT PARTICLE); TROMETHAMINE; POLYGLYCERYL-10 LAURATE; OCTYLDODECANOL; TRIHYDROXYSTEARIN; ALUMINUM OXIDE; SILICON DIOXIDE; PHENOXYETHANOL; ETHYLHEXYLGLYCERIN; TITANIUM DIOXIDE; FERRIC OXIDE RED; LAVENDER OIL; PELARGONIUM GRAVEOLENS FLOWER OIL

Radiant Shield Tinted Mineral Sunscreen SPF 40

Active Ingredient

Zinc Oxide 17%

Purpose

Sunscreen

Uses

Helps prevent sunburn

Warnings

For external use only.

Do not use

on damaged or broken skin.

When using this product

keep out of eyes. Rinse with water to remove.

Stop use and ask a doctor if

rash occurs.

Keep out of reach of children.

If swallowed, get medical help or contact a Poison Control Center right away.

Directions

• Apply liberally and evenly 15 minutes before sun exposure. • Reapply: at least every 2 hours • Use a water-resistant sunscreen if swimming or sweating. • Sun Protection Measures.Spending time in the sun increases your risk of skin cancer and early skin aging. To decrease this risk, regularly use a sunscreen with Broad Spectrum SPF value of 15 or higher and other sun protection measures including: • limit time in the sun, especially from 10 a.m.–2 p.m. • wear long-sleeved shirts, pants, hats and sunglasses • Children under 6 months of age: Ask a doctor.

Other Information

Protect the product in this container from excessive heat and direct sun.

Inactive Ingredients

Water (Aqua), Isododecane, Propanediol, Caprylic /Capric Triglyceride, Polyglyceryl-6 Polyricinoleate, C12-15 Alkyl Benzoate, Dimethicone, Polymethylsilsesquioxane/Trimethylsiloxysilicate, Coco-Caprylate/Caprate, Ethylhexyl Palmitate, Polymethylsilsesquioxane, Disteardimonium Hectorite, Polyglyceryl-10 Dioleate, Polyhydroxystearic Acid, Lecithin, Ectoin, Dimethylmethoxy Chromanol, Betula Alba (Birch) Bark Extract, Boswellia Serrata (Indian Frankincense) Extract, Polygonum Cuspidatum (Japanese Knotweed) Root Extract, Centella Asiatica (Gotu Kola) Extract, Butyrospermum Parkii (Shea) Butter, Glycerin, Tapioca Starch Polymethylsilsesquioxane, Propylene Carbonate, Polysilicone-11, Tromethamine, Polyglyceryl-10 Laurate, Octyldodecanol, Jojoba Esters, Trihydroxystearin, Alumina, Silica, Phenoxyethanol, Ethylhexylglycerin, Titanium Dioxide (CI 77891), Iron Oxide (CI 77491, CI 77492), Lavandula Angustifolia (Lavender) Oil, Pelargonium Graveolens (Rose Geranium) Flower Oil.